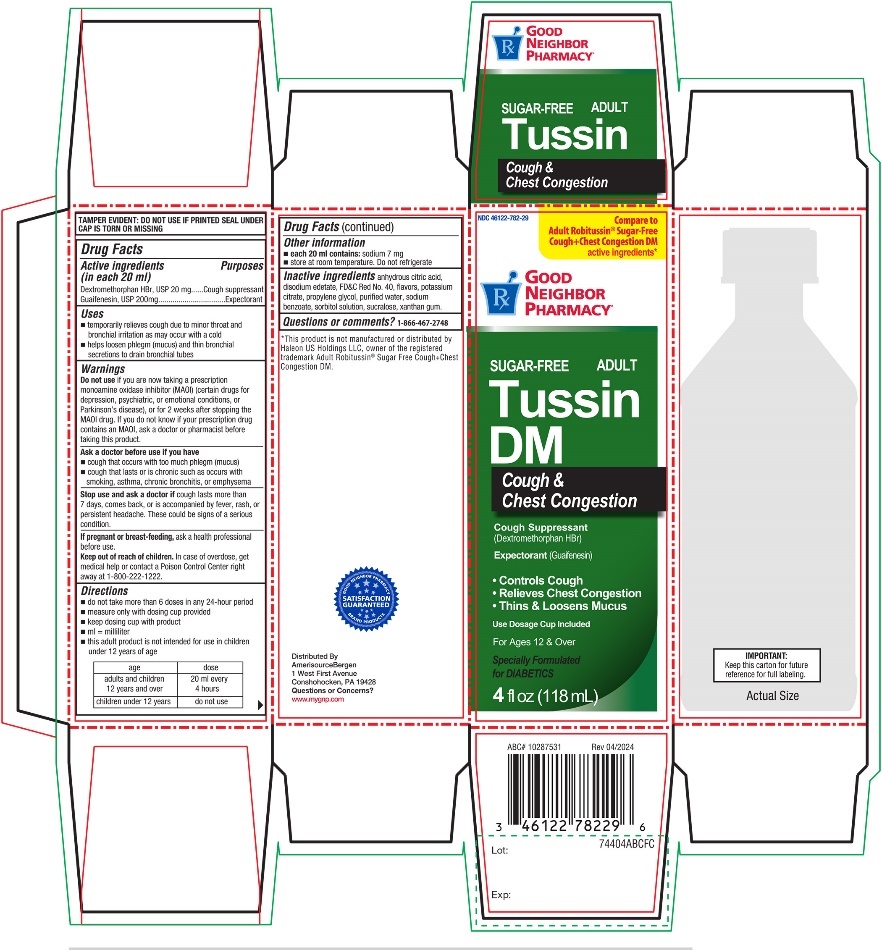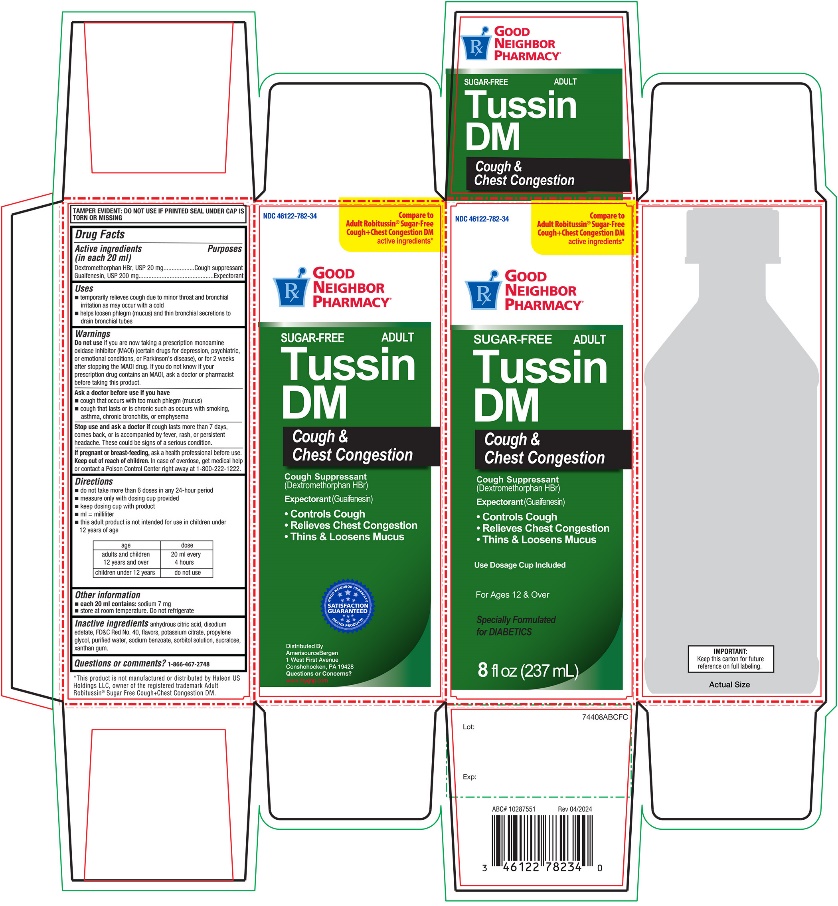 DRUG LABEL: Good Neighbor Sugar Free Adult Tussin DM

NDC: 46122-782 | Form: SOLUTION
Manufacturer: AMERISOURCE BERGEN
Category: otc | Type: HUMAN OTC DRUG LABEL
Date: 20250710

ACTIVE INGREDIENTS: DEXTROMETHORPHAN HYDROBROMIDE 20 mg/20 mL; GUAIFENESIN 200 mg/20 mL
INACTIVE INGREDIENTS: ANHYDROUS CITRIC ACID; EDETATE DISODIUM; FD&C RED NO. 40; POTASSIUM CITRATE; PROPYLENE GLYCOL; WATER; SODIUM BENZOATE; SORBITOL; SUCRALOSE; XANTHAN GUM

Good Neighbor SUGAR-FREE Adult Tussin DM Drug Facts

Active ingredients (in each 20 mL)

Dextromethorphan HBr, USP 20 mg

Guaifenesin, USP 200 mg

Purposes

Cough suppressant

Expectorant

Uses

- temporarily relieves cough due to minor throat and bronchial irritation as may occur with a cold
- helps loosen phlegm (mucus) and thin bronchial secretions to drain bronchial tubes

Do not use

if you are now taking a prescription monoamine oxidase inhibitor (MAOI) (certain drugs for depression, psychiatric, or emotional conditions, or Parkinson’s disease), or for 2 weeks after stopping the MAOI drug. If you do not know if your prescription drug contains an MAOI, ask a doctor or pharmacist before taking this product.

Ask a doctor before use if you have

- cough that occurs with too much phlegm (mucus)
- cough that lasts or is chronic such as occurs with smoking, asthma, chronic bronchitis, or emphysema

Stop use and ask a doctor if

cough lasts for more than 7 days, comes back, or is accompanied by fever, rash, or persistent headache. A persistent cough may be a sign of a serious condition.

If pregnant or breast-feeding,

ask a health professional before use.

Keep out of reach of children.

In case of overdose, get medical help or contact a Poison Control Center right away at 1-800-222-1222.

Directions

- do not take more than 6 doses in any 24-hour period
- measure only with dosing cup provided
- keep dosing cup with product
- mL = milliliter
- this adult product is not intended for use in children under 12 years of age

age | dose
adults and children 12 years and over | 20 mL every 4 hours
children under 12 years | do not use

Other information

- each 20 ml contains:sodium 7 mg
- store at room temperature. Do not refrigerate.

Inactive ingredients

anhydrous citric acid, edetate disodium, FD&C Red No. 40, flavor, potassium citrate, propylene glycol, purified water, sodium benzoate, sorbitol solution, sucralose, xanthan gum.

Questions or comments?

1-866-467-2748

Package/Label Principal Display Panel

Compare to Adult Robitussin® Sugar-Free Cough + Chest Congestion DM active ingredients*

NDC 46122-782-29

GOOD NEIGHBOR PHARMACY®

SUGAR FREE

Adult Tussin DM

Cough & Chest Congestion

Cough Suppressant (Dextromethorphan HBr)

Expectorant (Guaifenesin)

- Controls cough
- Relieves Chest Congestion
- Thins & Loosens Mucus

Specially Formulated for DIABETICS

Use Dosage Cup Included

For Ages 12 & Over

4 FL OZ (118 mL)

IMPORTANT:Keep this carton for future reference for full labeling.

TAMPER EVIDENT: DO NOT USE IF PRINTED SEAL UNDER CAP IS TORN OR MISSING.

Distributed By:

AmerisourceBergen

1 West First Avenue

Conshohocken, PA 19428

Questions or Concerns?

www.mygnp.com

*This product is not manufactured or distributed by Haleon US Holdings LLC, owner of the registered trademark Adult Robitussin®Sugar Free Cough + Congestion DM.

PACKAGE LABEL FOR 4 FL OZ (118 mL)